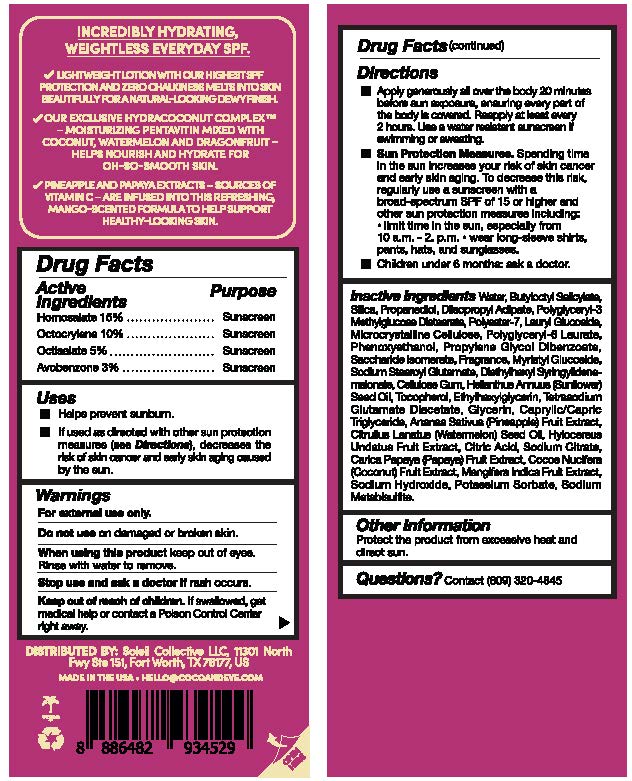 DRUG LABEL: Coco and Eve Sunny Honey Protect SPF 50
NDC: 85624-002 | Form: LOTION
Manufacturer: Soleil Collective LLC
Category: otc | Type: HUMAN OTC DRUG LABEL
Date: 20250826

ACTIVE INGREDIENTS: OCTISALATE 5 g/100 g; AVOBENZONE 3 g/100 g; OCTOCRYLENE 10 g/100 g; HOMOSALATE 15 g/100 g
INACTIVE INGREDIENTS: WATER; PHENOXYETHANOL; LAURYL GLUCOSIDE; PROPANEDIOL; CARICA PAPAYA (PAPAYA) FRUIT; SODIUM METABISULFITE; MYRISTYL GLUCOSIDE; COCOS NUCIFERA (COCONUT) FRUIT; DIISOPROPYL ADIPATE; POLYGLYCERYL-3 METHYLGLUCOSE DISTEARATE; POLYESTER-7; TOCOPHEROL; TETRASODIUM GLUTAMATE DIACETATE; GLYCERIN; SODIUM HYDROXIDE; POTASSIUM SORBATE; MICROCRYSTALLINE CELLULOSE; HELIANTHUS ANNUUS (SUNFLOWER) SEED OIL; SILICA; SODIUM CITRATE; BUTYLOCTYL SALICYLATE; POLYGLYCERYL-6 LAURATE; SACCHARIDE ISOMERATE; SODIUM STEAROYL GLUTAMATE; DIETHYLHEXYL SYRINGYLIDENEMALONATE; CELLULOSE GUM; ETHYLHEXYLGLYCERIN; CAPRYLIC/CAPRIC TRIGLYCERIDE; ANANAS SATIVUS (PINEAPPLE) FRUIT; CITRULLUS LANATUS (WATERMELON) SEED OIL; HYLOCEREUS UNDATUS FRUIT; CITRIC ACID; MANGIFERA INDICA (MANGO) FRUIT; PROPYLENE GLYCOL DIBENZOATE

Coconut Milk Body SPF 50 (85624-002-20)

Drug Facts

Active ingredients

Homosalate 15%
Octocrylene 10%
Octisalate 5%
Avobenzone 3%

Purpose

Sunscreen

Uses

• Helps prevent sunburn.
• If used as directed with other sun protection measures (see Directions), decreases the risk of skin cancer and early skin aging caused by the sun.

Warnings

For external use only

Do not use

on damaged skin or broken skin

When using this product

keep out of eyes. Rince with water to remove.

Stop use and ask a doctor

if rash occurs

Keep out of reach of children.

If swallowed, get medical help or contact a Poison Control Center right away.

Directions

• Shake well before use. Apply generously all over the body 20 minutes before sun exposure, ensuring every part of the body is covered. Reapply after 40 minutes of swimming or sweating, immediately after towel drying and at least ever 2 hours.
• Sun Protection Measures. Spending time in the sun increases your risk of skin cancer and early skin aging. To decrease this risk, regularly use sunscreen with a broad-spectrum SPF of 15 or higher and other sun protection measures including: • limit time in the sun, especially from 10 a.m. - 2 p.m. • Wear long-sleeved shirts, pants, hats, and sunglasses.
• Children under 6 months: ask a doctor.

Other information

Protect the product from excessive heat and direct sun.

Inactive ingredients

AQUA (WATER, EAU), BUTYLOCTYL SALICYLATE, SILICA, PROPANEDIOL, DIISOPROPYL ADIPATE, POLYGLYCERYL-3 METHYLGLUCOSE DISTEARATE, POLYESTER-7, LAURYL GLUCOSIDE, MICROCRYSTALLINE CELLULOSE, POLYGLYCERYL-6 LAURATE, PHENOXYETHANOL, PROPYLENE GLYCOL DIBENZOATE, SACCHARIDE ISOMERATE, PARFUM (FRAGRANCE), MYRISTYL GLUCOSIDE, SODIUM STEAROYL GLUTAMATE, DIETHYLHEXYL SYRINGYLIDENEMALONATE, CELLULOSE GUM, HELIANTHUS ANNUUS (SUNFLOWER) SEED OIL, TOCOPHEROL, ETHYLHEXYLGLYCERIN, TETRASODIUM GLUTAMATE DIACETATE, GLYCERIN, CAPRYLIC/CAPRIC TRIGLYCERIDE, ANANAS SATIVUS (PINEAPPLE) FRUIT EXTRACT, CITRULLUS LANATUS (WATERMELON) SEED OIL, HYLOCEREUS UNDATUS FRUIT EXTRACT, CITRIC ACID, SODIUM CITRATE, CARICA PAPAYA (PAPAYA) FRUIT EXTRACT, COCOS NUCIFERA (COCONUT) FRUIT EXTRACT, MANGIFERA INDICA FRUIT EXTRACT, SODIUM HYDROXIDE, POTASSIUM SORBATE, SODIUM METABISULFITE.

Questions?

Contact (609) 320-4845